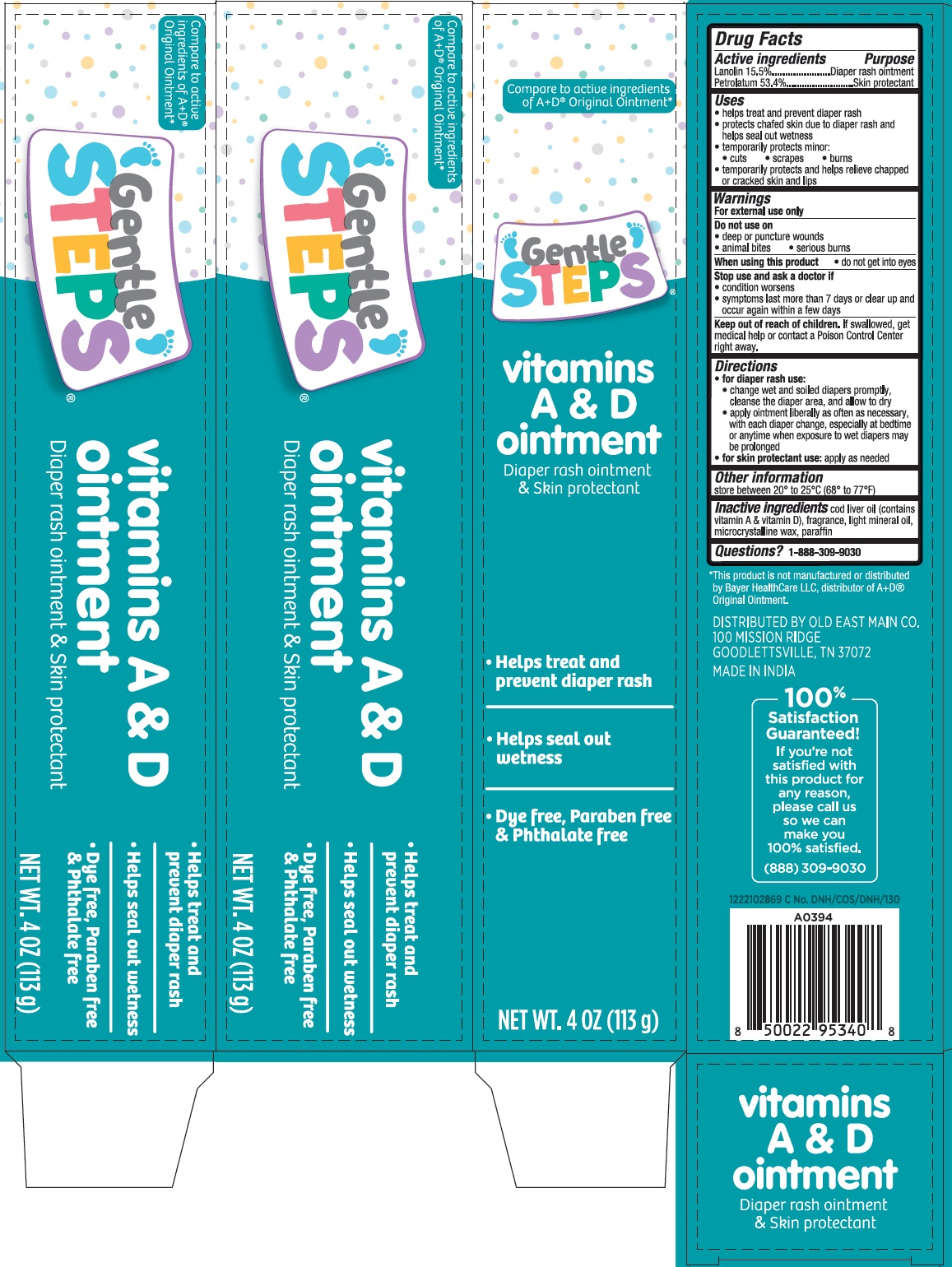 DRUG LABEL: Gentle STEPS vitamins A and D Diaper Rash and Skin Protectant
NDC: 55910-805 | Form: OINTMENT
Manufacturer: Old East Main CO.
Category: otc | Type: HUMAN OTC DRUG LABEL
Date: 20241011

ACTIVE INGREDIENTS: LANOLIN 15.5 g/100 g; PETROLATUM 53.4 g/100 g
INACTIVE INGREDIENTS: COD LIVER OIL; LIGHT MINERAL OIL; MICROCRYSTALLINE WAX; PARAFFIN

Gentle STEPS® vitamins A & D Diaper Rash Ointment & Skin Protectant

Active ingredients

Lanolin 15.5%
Petrolatum 53.4%

Purpose

Diaper rash ointment
Skin protectant

Uses

• helps treat and prevent diaper rash
• protects chafed skin due to diaper rash and helps seal out wetness
• temporarily protects minor:
• cuts • scrapes • burns
• temporarily protects and helps relieve chapped or cracked skin and lips

Warnings

For external use only

Do not use on
• deep or puncture wounds
• animal bites • serious burns

When using this product • do not get into eyes

Stop use and ask a doctor if
• condition worsens
• symptoms last more than 7 days or clear up and occur again within a few days

Keep out of reach of children. If swallowed, get medical help or contact a Poison Control Center right away.

Directions

• for diaper rash use:
• change wet and soiled diapers promptly, cleanse the diaper area, and allow to dry
• apply ointment liberally as often as necessary, with each diaper change, especially at bedtime or anytime when exposure to wet diapers may be prolonged
• for skin protectant use: apply as needed

Other information

store between 20° to 25°C (68° to 77°F)

Inactive ingredients

cod liver oil (contains vitamin A & vitamin D), fragrance, light mineral oil, microcrystalline wax, paraffin

Questions?

1-888-309-9030

Compare to active ingredients of A+D® Original Ointment*

• Helps treat and prevent diaper rash

• Helps seal out wetness

• Dye free, Paraben free & Phthalate free

*This product is not manufactured or distributed by Bayer HealthCare LLC, distributor of A+D® Original Ointment.

DISTRIBUTED BY OLD EAST MAIN CO.
100 MISSION RIDGE
GOODLETTSVILLE, TN 37072
MADE IN INDIA

100% Satisfaction Guaranteed!

If you're not satisfied with this product for any reason, please call us so we can make you 100% satisfied.

(888) 309-9030